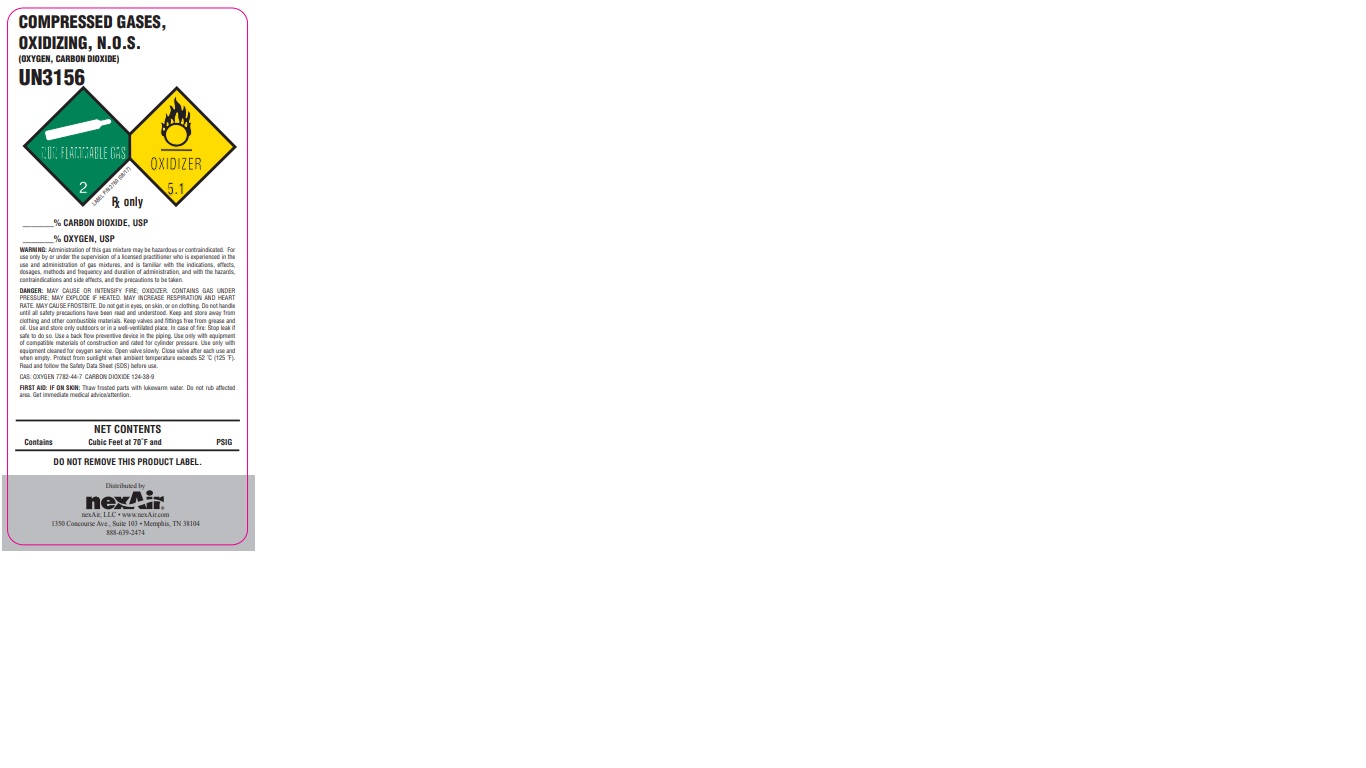 DRUG LABEL: Carbon Dioxide/Oxygen Mix
NDC: 12213-800 | Form: GAS
Manufacturer: NEXAIR, LLC
Category: prescription | Type: HUMAN PRESCRIPTION DRUG LABEL
Date: 20251031

ACTIVE INGREDIENTS: OXYGEN 50 mL/1 L
INACTIVE INGREDIENTS: CARBON DIOXIDE 950 mL/1 L

carbon dioxide/oxygen mix

PACKAGE LABEL

COMPRESSED GASES, OXIDIZING, N.O.S (OXYGEN, CARBON DIOXIDE)

UN3156

RX only

% CARBON DIOXIDE, USP

% OXYGEN, USP

WARNING: Administration of this gas mixture may be hazardous or contraindicated. For use only by or under the supervision of a licensed practitioner who is experienced in the use and administration of gas mixtures, and is familiar with the indications, effects, dosages, methods and frequency and duration of administration, and with the hazards, contraindications and side effects, and the precautions to be taken.

DANGER: MAY CAUSE OR INTENSIFY FIRE; OXIDIZER. CONTAINS GAS UNDER PRESSURE; MAY EXPLODE IF HEATED. MAY INCREASE RESPIRATION AND HEART RATE. MAY CAUSE FROSTBITE. Do not get in eyes, on skin, or on clothing. Do not handle until all safety precautions have been read and understood. Keep and store away from clothing and other combustible materials. Keep valves and fittings free from grease and oil. Use and store only outdoors or in a well-ventilated place. Use only with equipment of compatible materials of construction and rated for cylinder pressure. Use only with equipment cleaned for oxygen service. Open valve slowly. Close valve after each use and when empty. Protect from sunlight when ambient temperature exceeds 52 C (125 F). Read and follow the Safety Data Sheet (SDS) before use.

CAS: OXYGEN 7782-44-7 CARBON DIOXIDE 124-38-9

FIRST AID: IF ON SKIN: Thaw frosted parts with lukewarm water. Do not rub affected area. Get immediate medical advice/attention.

NET CONTENTS

Contains Cubic Feet at 70 F and PSIG

DO NOT REMOVE THIS PRODUCT LABEL.

Distributed by nexAir

nexAir, LLC www.nexAir.com

1350 Concourse Ave., Suite 103 Memphis, TN 38104

888-639-2474